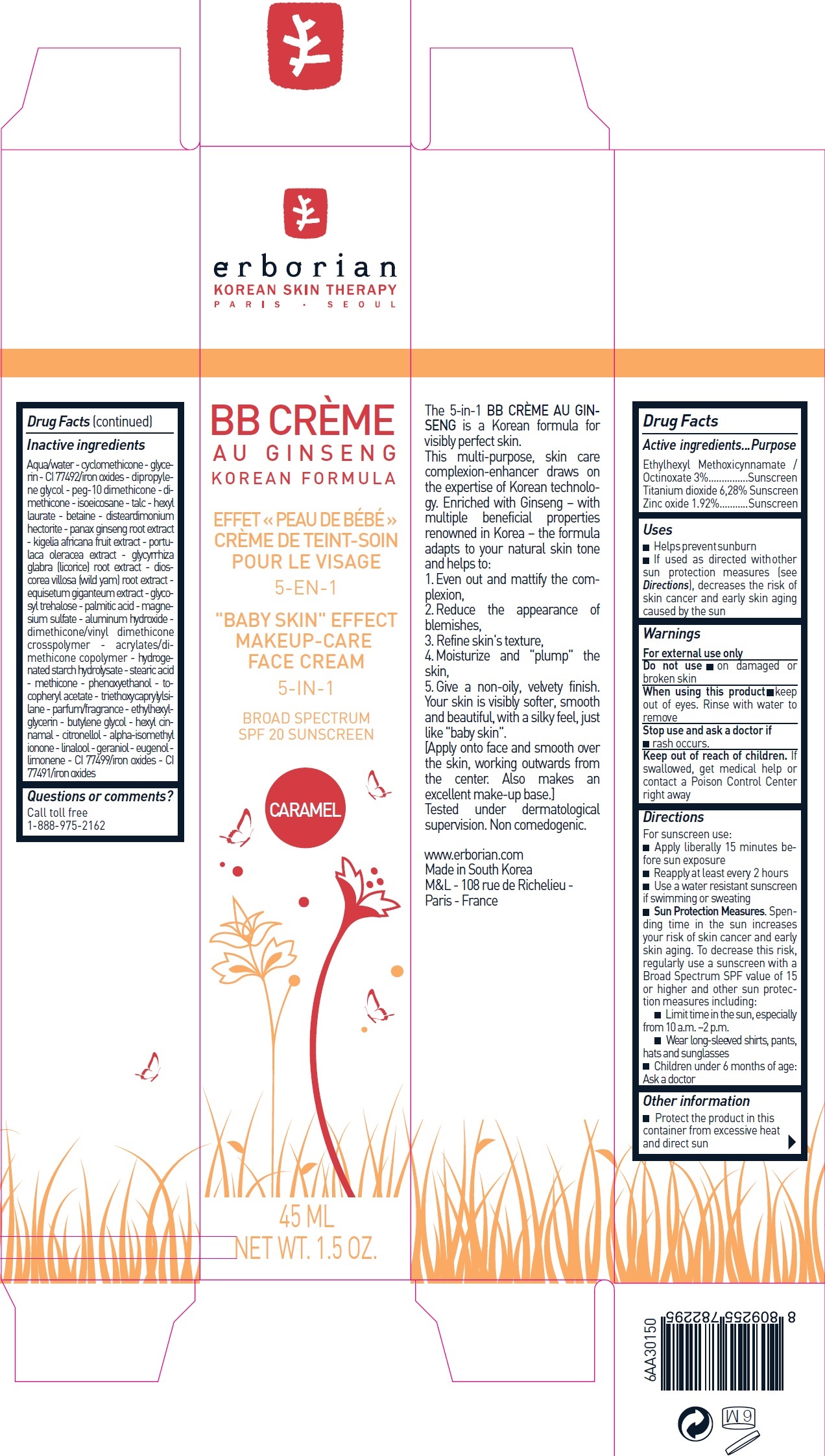 DRUG LABEL: ERBORIAN - BB CREME AU GINSENG CARAMEL SPF20
NDC: 10345-903 | Form: CREAM
Manufacturer: LABORATOIRES M&L
Category: otc | Type: HUMAN OTC DRUG LABEL
Date: 20231209

ACTIVE INGREDIENTS: OCTINOXATE 30 mg/1 mL; TITANIUM DIOXIDE 62.8 mg/1 mL; ZINC OXIDE 19.2 mg/1 mL
INACTIVE INGREDIENTS: WATER; CYCLOMETHICONE; GLYCERIN; FERRIC OXIDE YELLOW; DIPROPYLENE GLYCOL; PEG-10 DIMETHICONE (600 CST); DIMETHICONE; ISOEICOSANE; TALC; HEXYL LAURATE; BETAINE; DISTEARDIMONIUM HECTORITE; ASIAN GINSENG; KIGELIA AFRICANA FRUIT; PURSLANE; GLYCYRRHIZA GLABRA; DIOSCOREA VILLOSA TUBER; BEMISIOSE; PALMITIC ACID; MAGNESIUM SULFATE, UNSPECIFIED FORM; ALUMINUM HYDROXIDE; HYDROGENATED STARCH HYDROLYSATE; STEARIC ACID; METHICONE (20 CST); PHENOXYETHANOL; .ALPHA.-TOCOPHEROL ACETATE; TRIETHOXYCAPRYLYLSILANE; ETHYLHEXYLGLYCERIN; BUTYLENE GLYCOL; .ALPHA.-HEXYLCINNAMALDEHYDE; .BETA.-CITRONELLOL, (R)-; ISOMETHYL-.ALPHA.-IONONE; LINALOOL, (+/-)-; GERANIOL; EUGENOL; LIMONENE, (+)-; FERROSOFERRIC OXIDE; FERRIC OXIDE RED

ERBORIAN - BB CREME AU GINSENG CARAMEL SPF20

Active ingredients

Ethylhexyl Methoxicynnamate / Octinoxate 3% Titanium dioxide 6,28% Zinc oxide 1.92%

Purpose

Sunscreen

Uses

- Helps prevent sunburn
- If used as directed with other sun protection measures (see), decreases the risk of skin cancer and early skin aging caused by the sun Directions

Warnings

For external use only

Do not use

- on damaged or broken skin

When using this product

- keep out of eyes. Rinse with water to remove

Stop use and ask a doctor if

- rash occurs.

Keep out of reach of children.

If swallowed, get medical help or contact a Poison Control Center right away

Directions

For sunscreen use:

- Apply liberally 15 minutes before sun exposure
- Reapply at least every 2 hours
- Use a water resistant sunscreen if swimming or sweating
- Spending time in the sun increases your risk of skin cancer and early skin aging. To decrease this risk, regularly use a sunscreen with a Broad Spectrum SPF value of 15 or higher and other sun protection measures including: Sun Protection Measures.
- Limit time in the sun, especially from 10 a.m. –2 p.m.
- Wear long-sleeved shirts, pants, hats and sunglasses
- Children under 6 months of age: Ask a doctor

Other information

- Protect the product in this container from excessive heat and direct sun

Inactive ingredients

Aqua/water - cyclomethicone - glycerin - CI 77492/iron oxides - dipropylene glycol - peg-10 dimethicone - dimethicone - isoeicosane - talc - hexyl laurate - betaine - disteardimonium hectorite - panax ginseng root extract - kigelia africana fruit extract - portulaca oleracea extract - lycyrrhiza glabra (licorice) root extract - dioscorea villosa (wild yam) root extract - equisetum giganteum extract - glycosyl trehalose - palmitic acid - magnesium sulfate - aluminum hydroxide - dimethicone/vinyl dimethicone crosspolymer - acrylates/dimethicone copolymer - hydrogenated starch hydrolysate - stearic acid - methicone - phenoxyethanol - tocopheryl acetate - triethoxycaprylylsilane - parfum/fragrance - ethylhexylglycerin - butylene glycol - hexyl cinnamal - citronellol - alpha-isomethyl ionone - linalool - geraniol - eugenol - limonene - CI 77499/iron oxides - CI 77491/iron oxides

Questions or comments?

Call toll free 1-888-975-2162